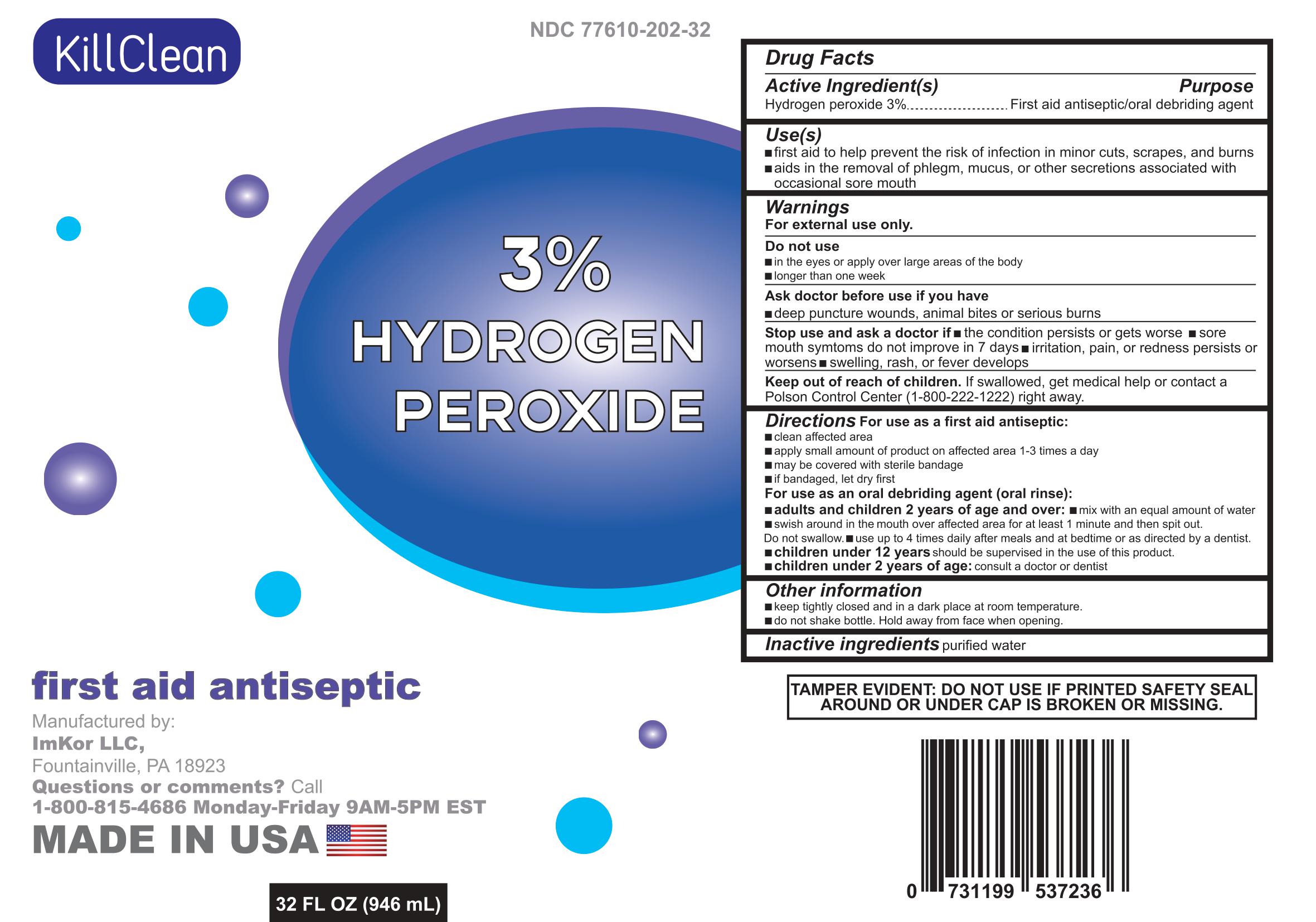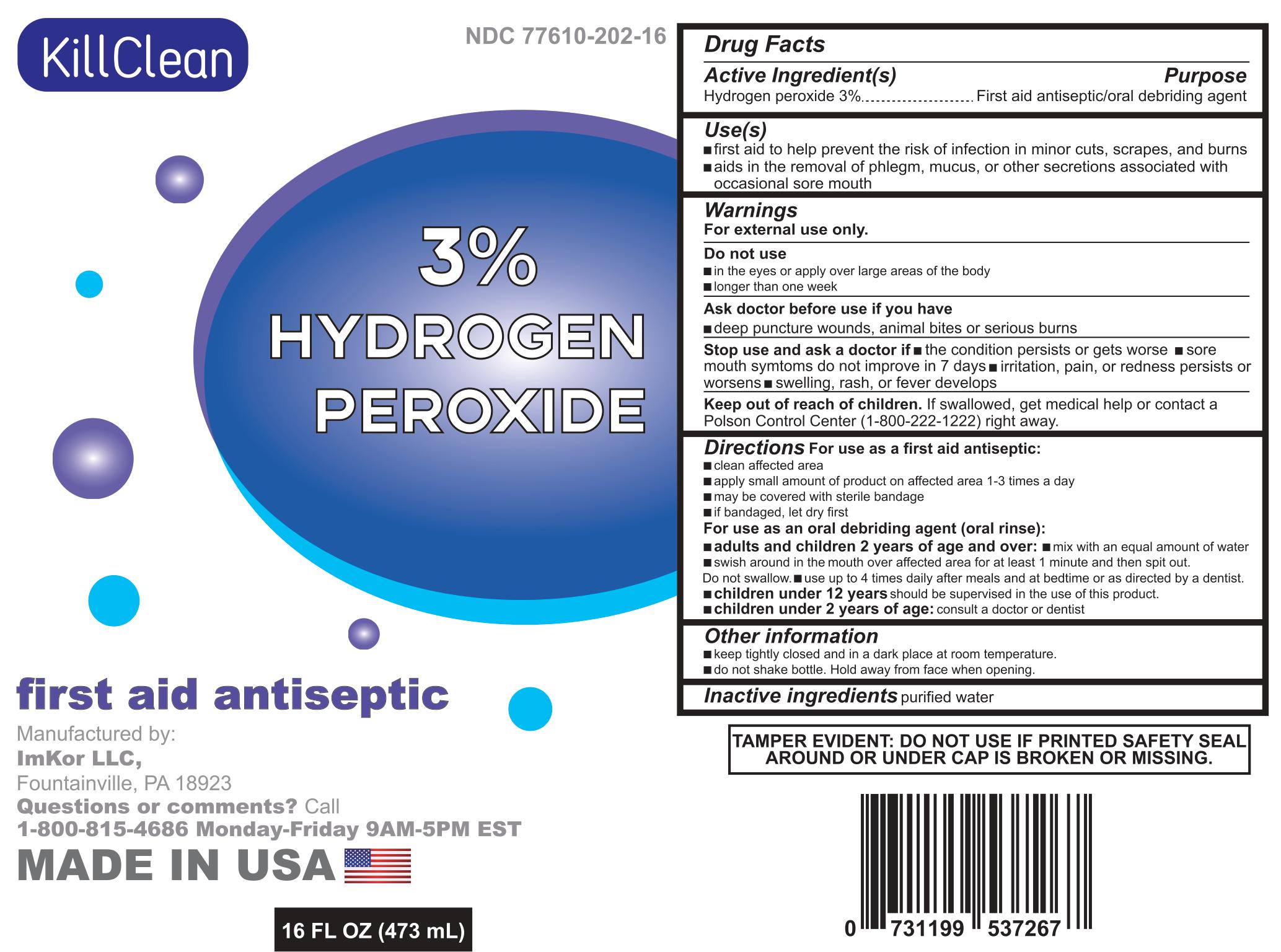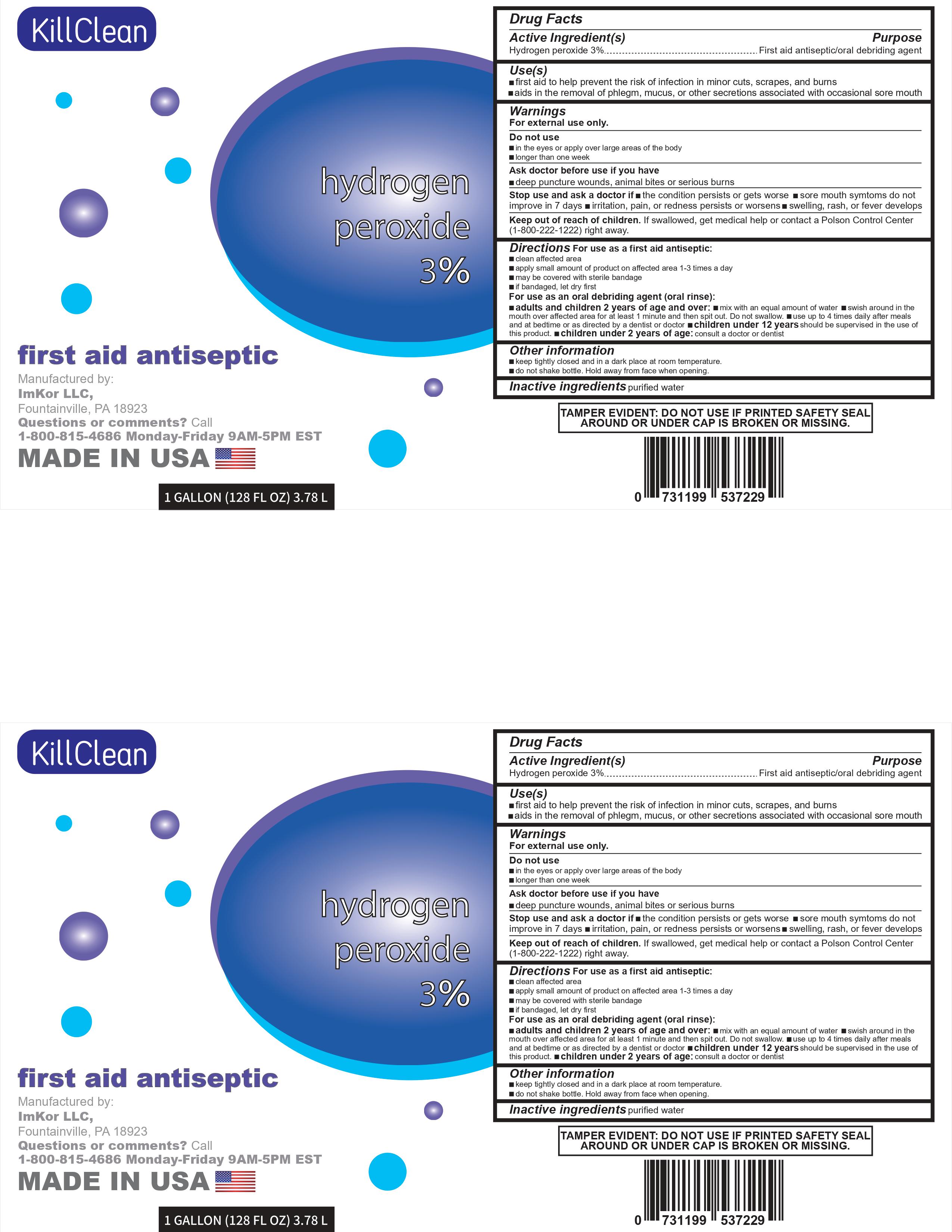 DRUG LABEL: Hydrogen Peroxide
NDC: 77610-202 | Form: LIQUID
Manufacturer: ImKor Limited Liability Company
Category: otc | Type: HUMAN OTC DRUG LABEL
Date: 20200914

ACTIVE INGREDIENTS: HYDROGEN PEROXIDE 0.03 L/0.03 L
INACTIVE INGREDIENTS: WATER

DOSAGE AND ADMINISTRATION

3.78L NDC: 77610-202-01

WARNINGS

3.78L NDC: 77610-202-01

INACTIVE INGREDIENT

3.78L NDC: 77610-202-01

INDICATIONS AND USAGE

3.78L NDC: 77610-202-01

KEEP OUT OF REACH OF CHILDREN

3.78L NDC: 77610-202-01

PURPOSE

3.78L NDC: 77610-202-01

ACTIVE INGREDIENT

3.78L NDC: 77610-202-01

PACKAGE LABEL

3.78 L NDC: 77610-202-01

473 mL NDC: 77610-202-16

946 mL NDC: 77610-202-32